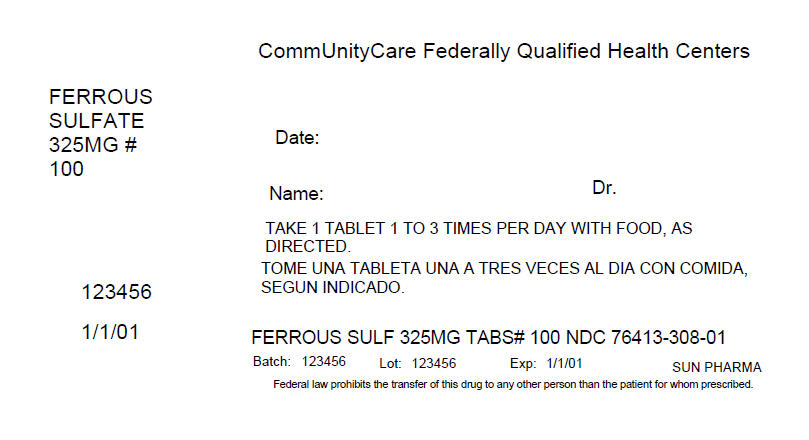 DRUG LABEL: Ferrous Sulfate
NDC: 76413-308 | Form: TABLET, FILM COATED
Manufacturer: Central Texas Community Health Centers
Category: otc | Type: Human OTC Drug Label
Date: 20160322

ACTIVE INGREDIENTS: FERROUS SULFATE 325 mg/1 1
INACTIVE INGREDIENTS: CELLULOSE, MICROCRYSTALLINE; DIBASIC CALCIUM PHOSPHATE DIHYDRATE; CROSCARMELLOSE SODIUM; SODIUM STARCH GLYCOLATE TYPE A POTATO; HYPROMELLOSES; STEARIC ACID; POLYETHYLENE GLYCOL 400; FD&C RED NO. 40; MAGNESIUM STEARATE; TITANIUM DIOXIDE; POLYETHYLENE GLYCOL 8000; CARNAUBA WAX

Ferrous Sulfate Film Coated Tablets

ACTIVE INGREDIENT(S)

EACH TABLET CONTAINS:

Amount per tablet | % Daily Value
Iron 65 mg | 361%
Dried Ferrous Sulfate, equivalent to 325 mg Ferrous Sulfate per tablet.

INACTIVE INGREDIENTS

Other ingredients for Red Tablets: microcrystalline cellulose, dibasic calcium phosphate dihydrate, croscarmellose sodium, sodium starch glycolate, hypromellose, stearic acid, polyethylene glycol (PEG) 400, FD&C red #40 aluminum lake, magnesium stearate, titanium dioxide, polyethylene glycol (PEG) 8000, carnauba wax
Other ingredients for Green Tablets: microcrystalline cellulose, dibasic calcium phosphate dihydrate, croscarmellose sodium, sodium starch glycolate, hypromellose, stearic acid, polyethylene glycol (PEG) 400, magnesium stearate, riboflavin, FD&C bule #1 aluminum lake, titanium dioxide, FD&C blue #2 aluminum lake, polyethylene glycol (PEG) 8000, FD&C red #40 aluminum lake, FD&C yellow #6 aluminum lake, carnauba wax

PURPOSE

Dietary Supplement

USE(S)

One tablet daily or as directed by a physician. For children under 12, consult a physician before using this product.

WARNINGS

Iron may interfere with absorpiton of certain antibiotics; these products should not be taken within two hours of each other.
Occasional gastrointestinal discomfort (such as nausea) may be minimized by taking iron with meals. Iron-containing products may occassionally cause constipation or diarrhea. If pregnant or nursing consult a physicial before using this product.

DO NOT USE

TAMPER EVIDENT: DO NOT USE THIS PRODUCT IF THE IMPRINTED FOIL SEAL OVER THE MOUTH OF THE BOTTLE IS CUT, TORN, BROKEN OR MISSING

OTHER REQUIRED WARNINGS

The information on this label has not been evaluated by the Food and Drug Administration. This product is not intended to diagnose, trea, cure or prevent any disease.

To report a serious adverse event or to obtain product information, contact 800-818-4555.

KEEP OUT OF REACH OF CHILDREN

WARNING: Accidental overdose of iron-containing products is a leading cause of fatal poisoning in children under 6. Keep this product out of reach of children. In case of accidental overdose, call a doctor or poison control center immediately.

DIRECTIONS

One tablet daily or as directed by a physician. For children under 12, consult a physical before using this product.
Do not exceed recommended dosage.
Do not use except under the advice and supervision of a physician.

STORAGE

Store at 25˚C (77˚F); excursions permitted between 15˚-30˚C (59˚-86˚F)

PRINCIPAL DISPLAY PANEL - 325 MG Tablet Bottle Label

CommUnityCare Federally Qualified Health Centers

FERROUS
SULFATE
325MG #
100

Date:

Name:
Dr.

TAKE 1 TABLET 1 TO 3 TIMES PER DAY WITH FOOD, AS
DIRECTED.

123456

1/1/01

FERROUS SULF 325MG TABS# 100 NDC 76413-308-01

Batch: 123456
Lot: 123456
Exp: 1/1/01
SUN PHARMA

Federal law prohibits the transfer of this drug to any other person than the patient for whom prescribed.